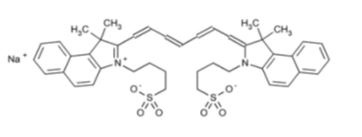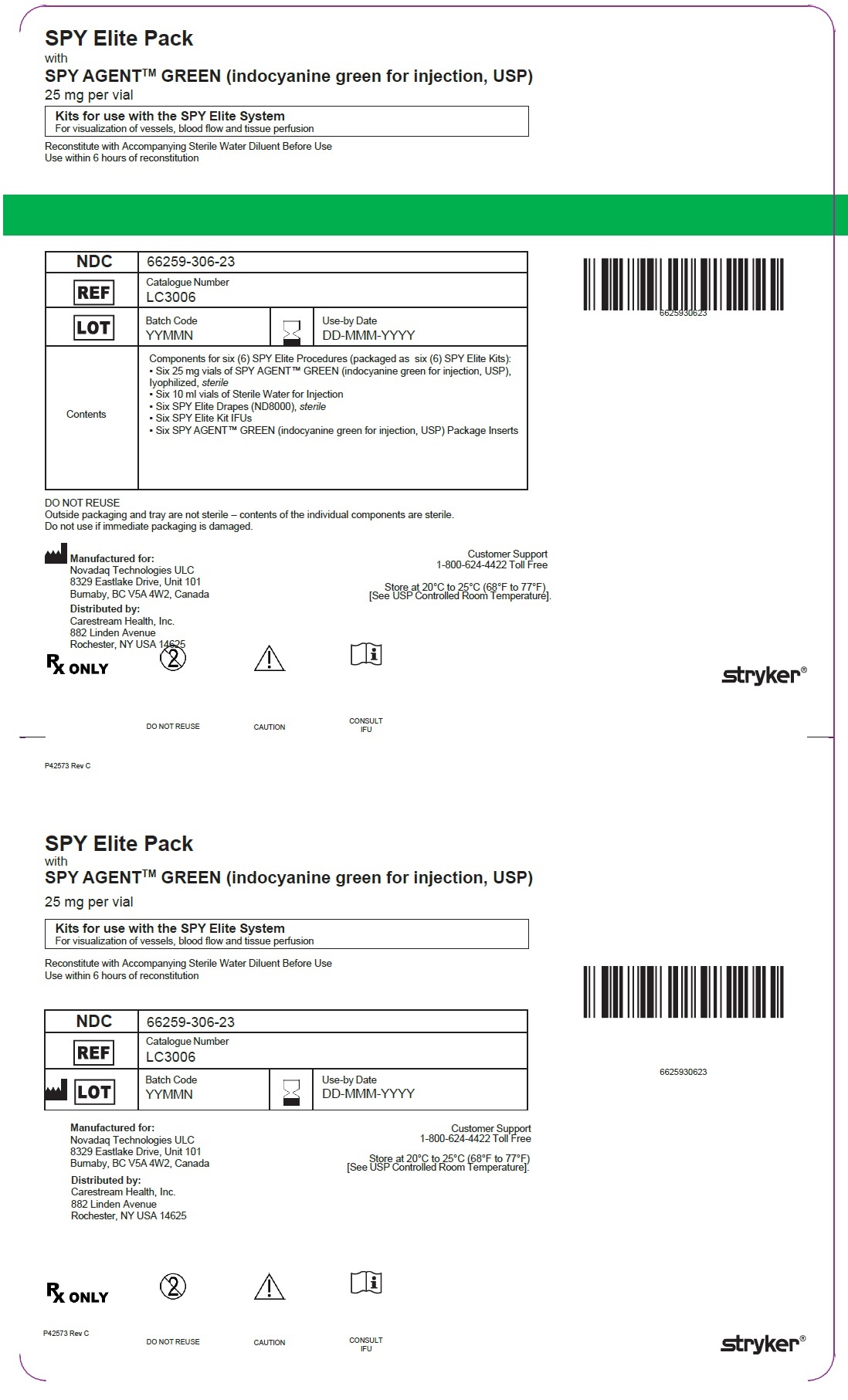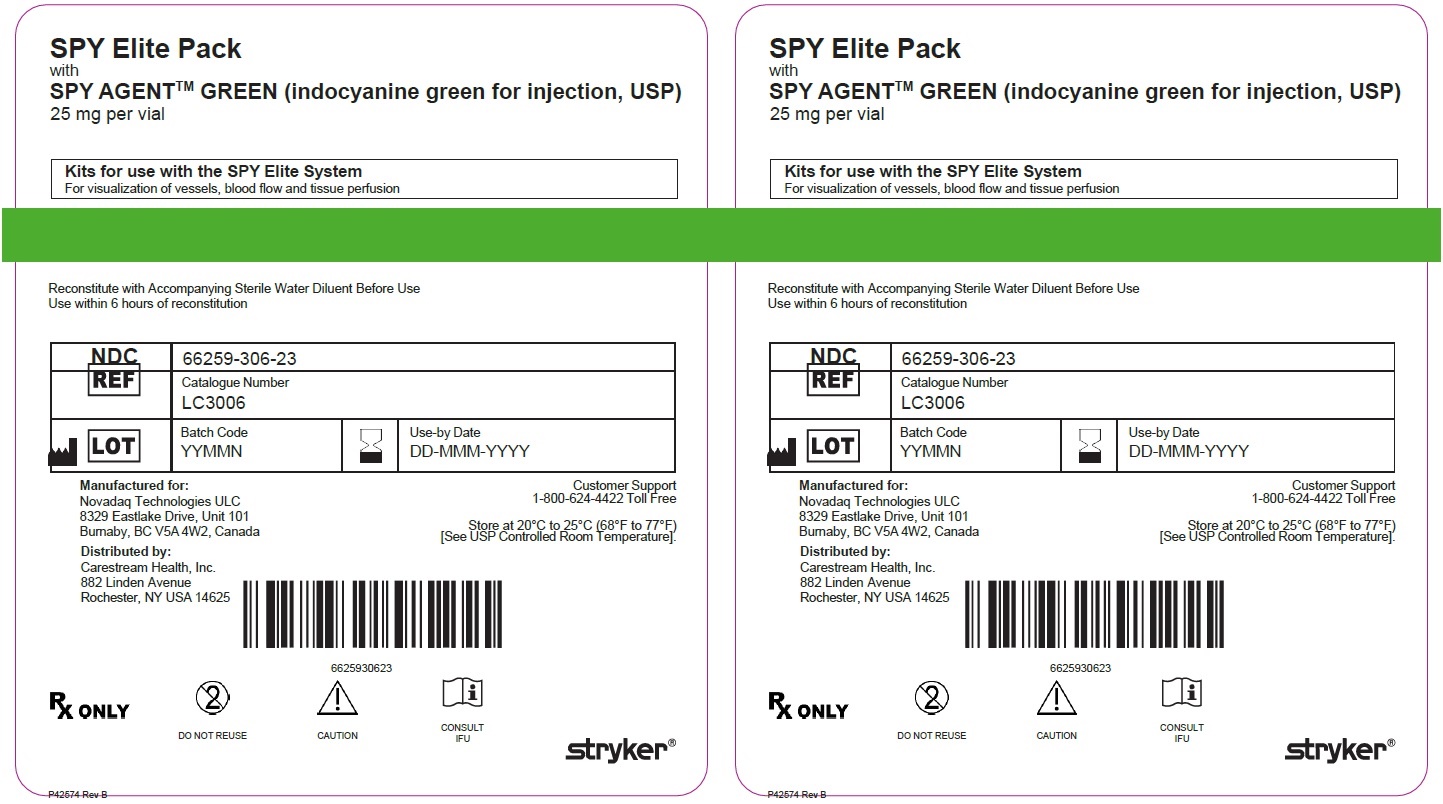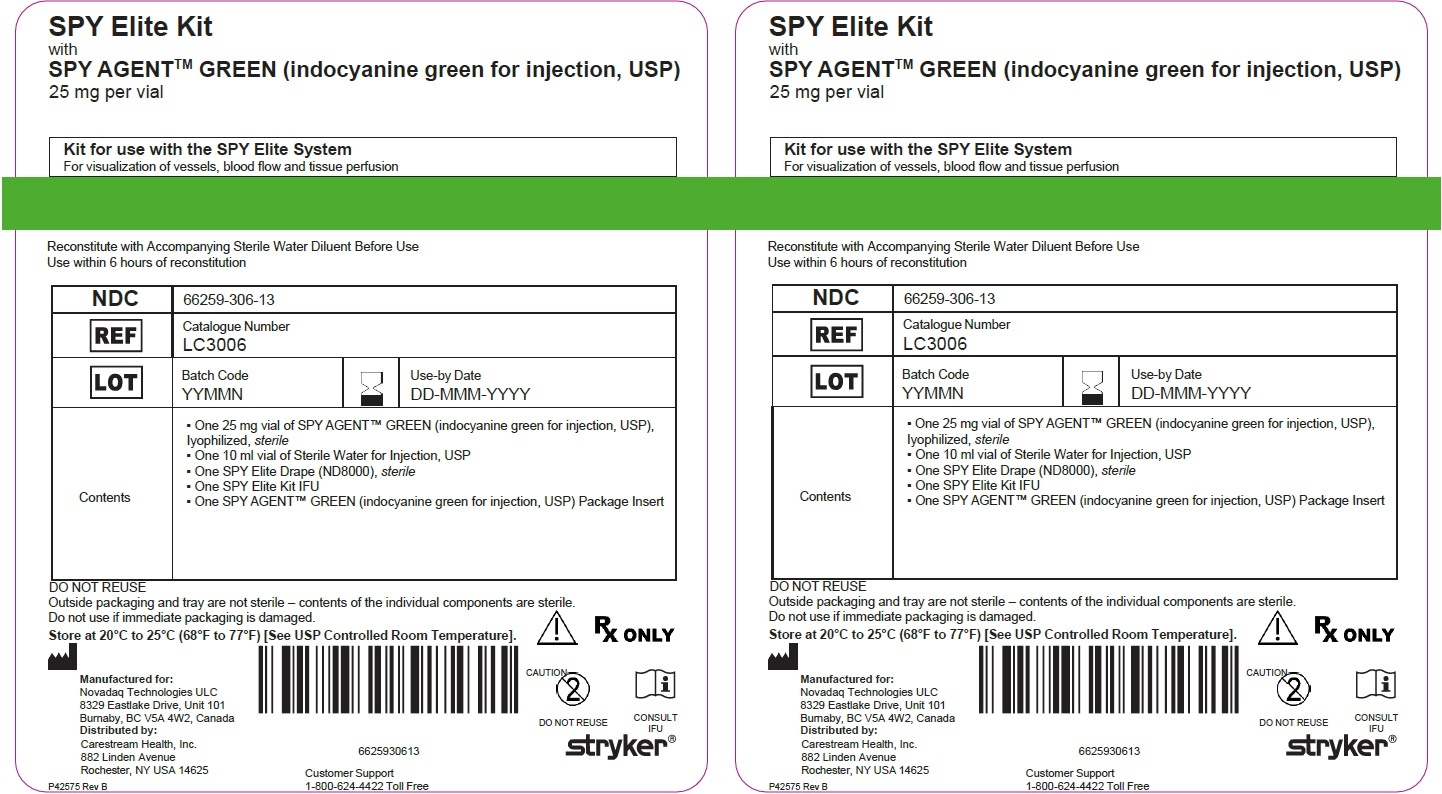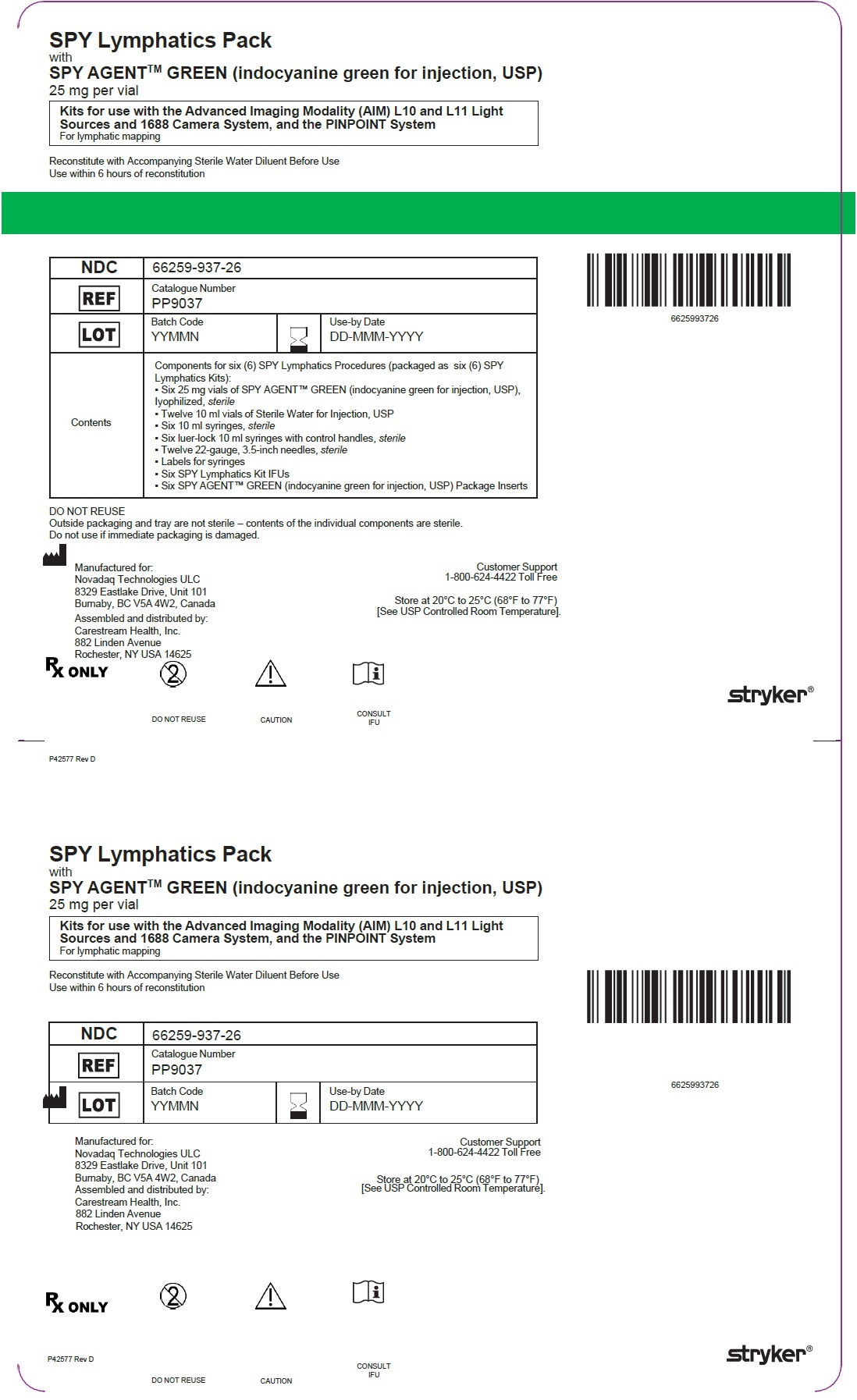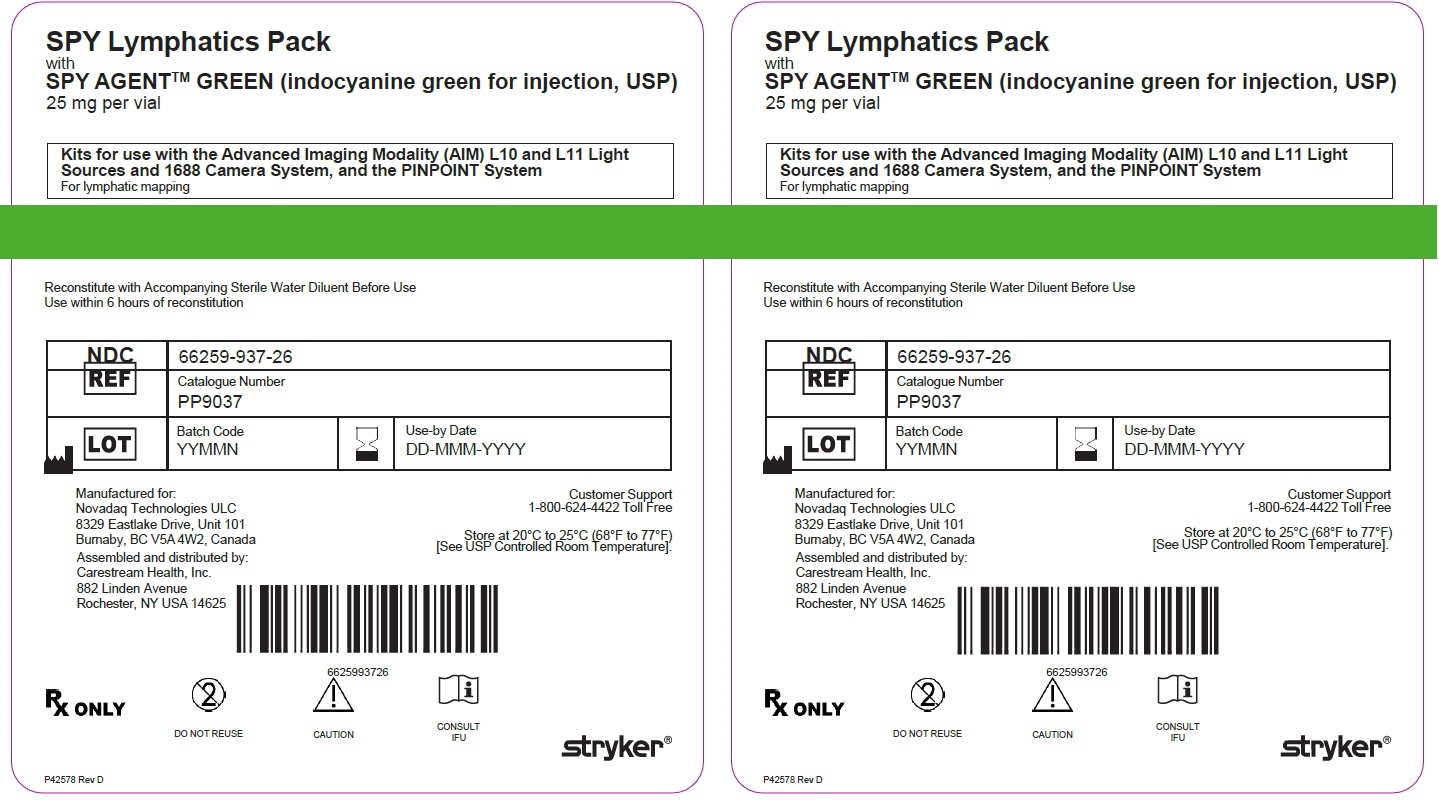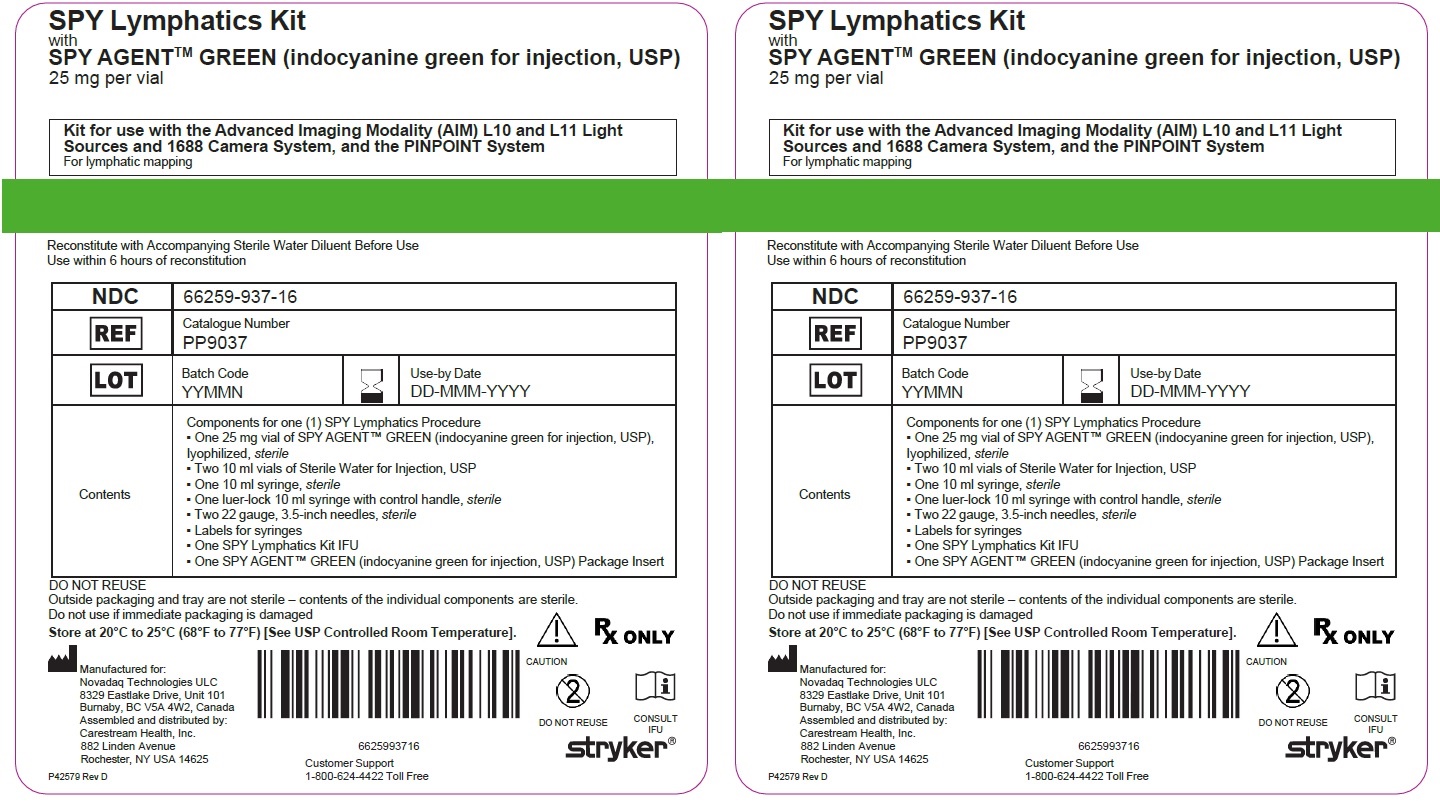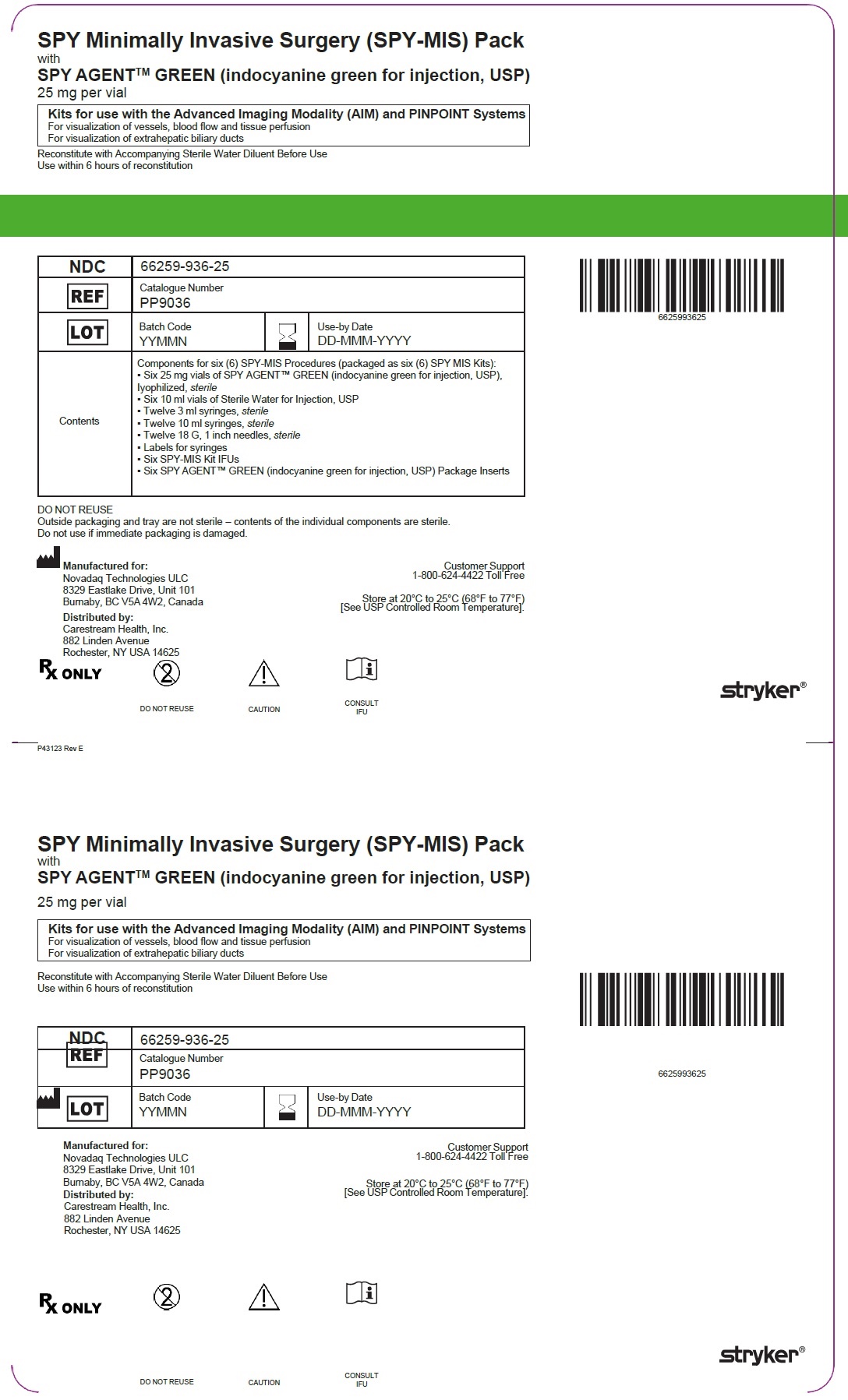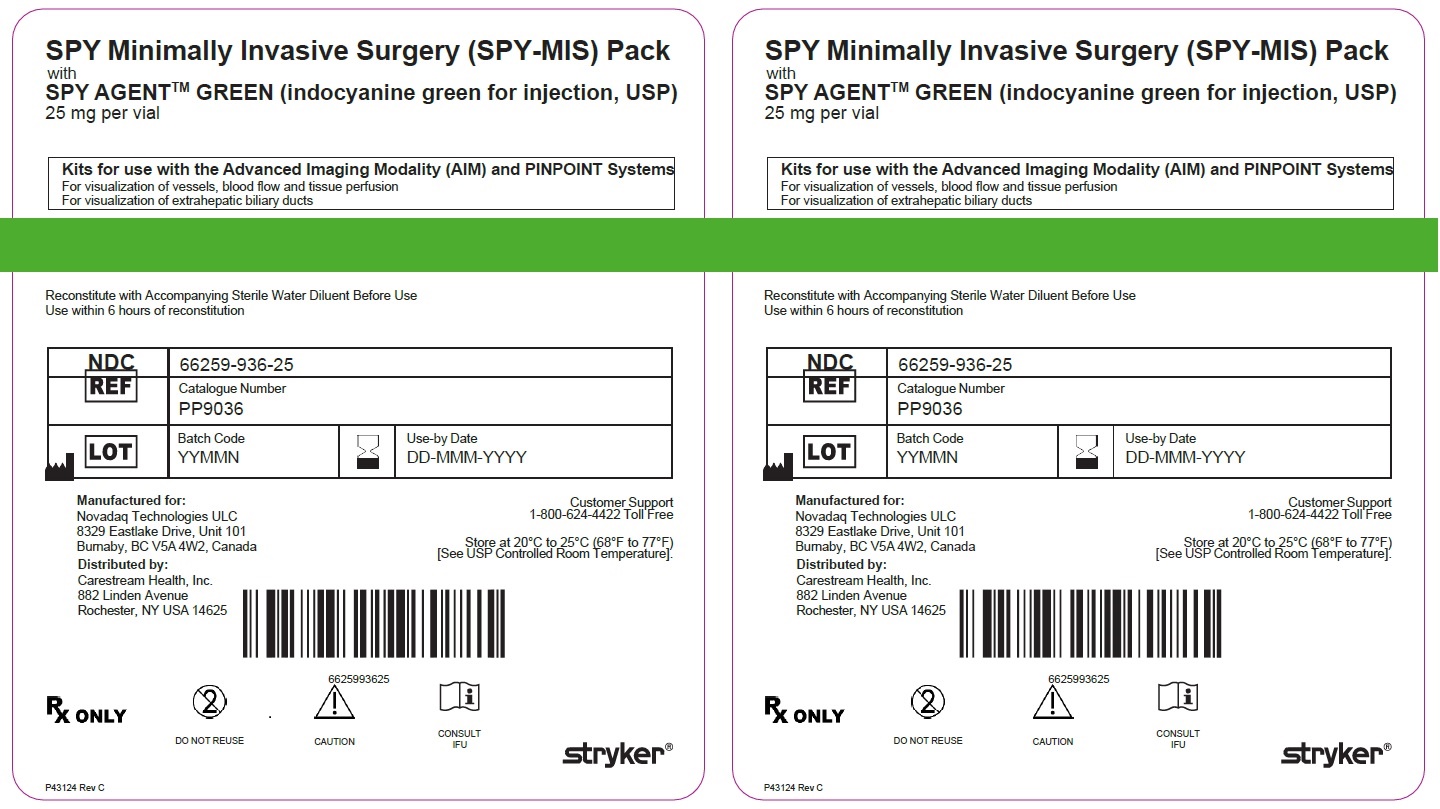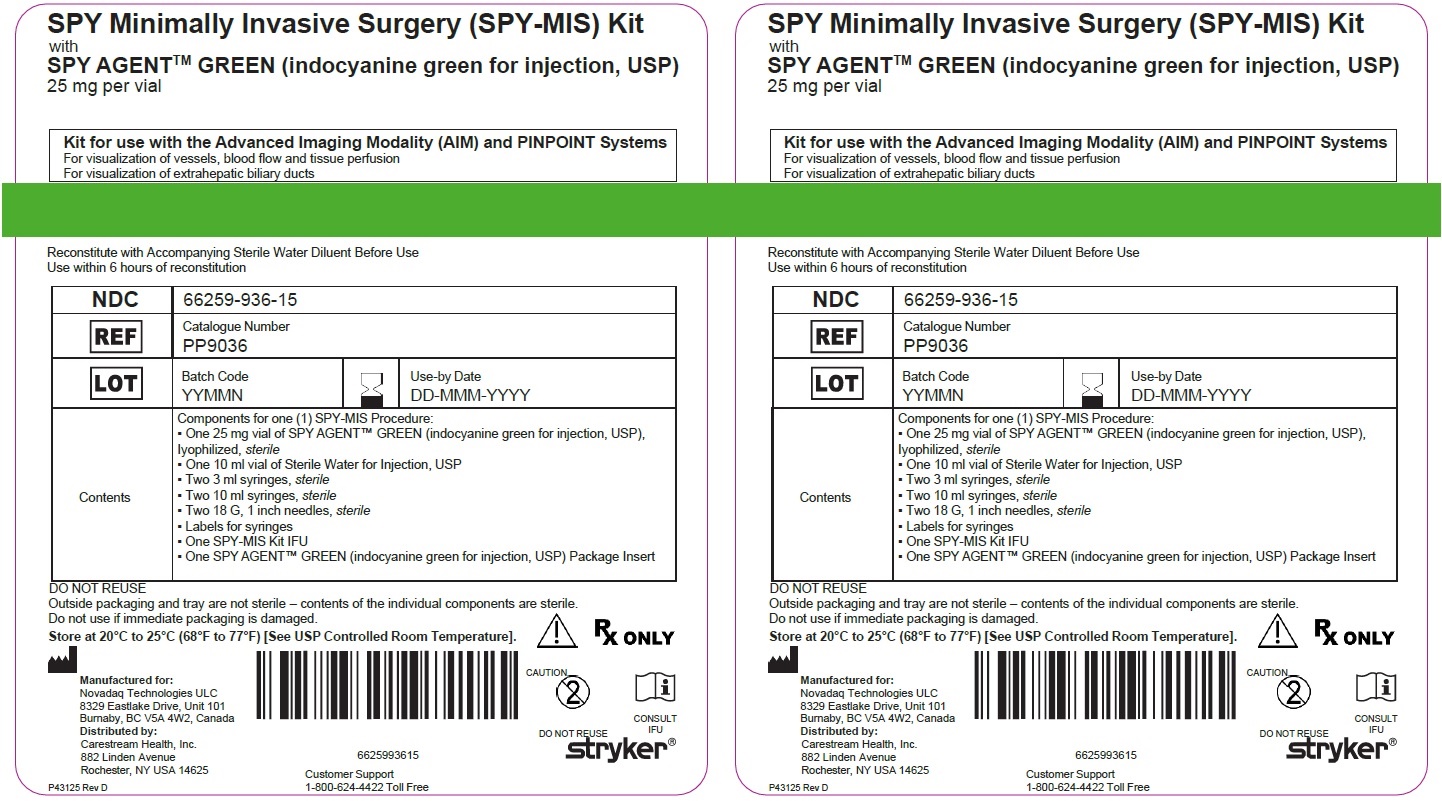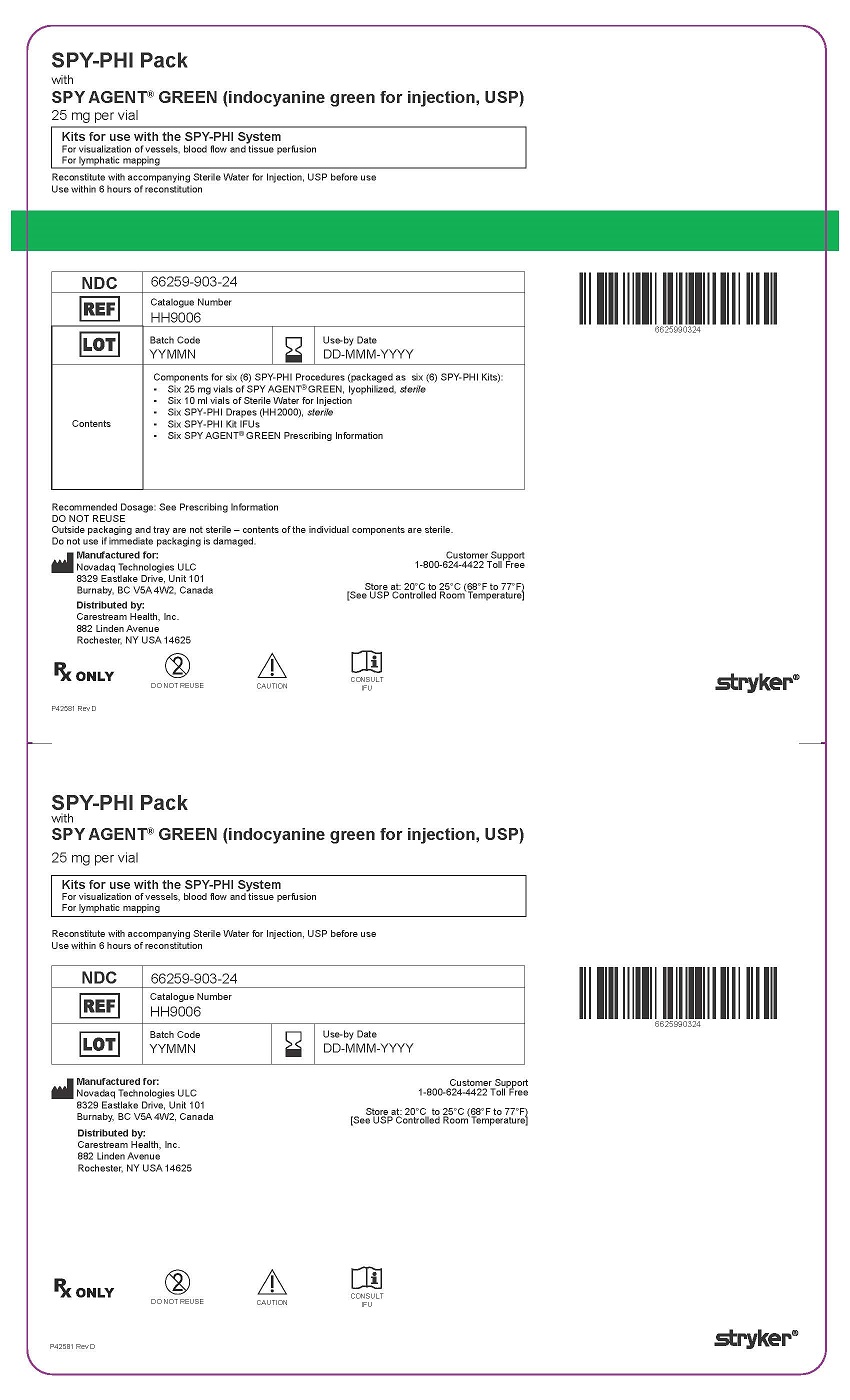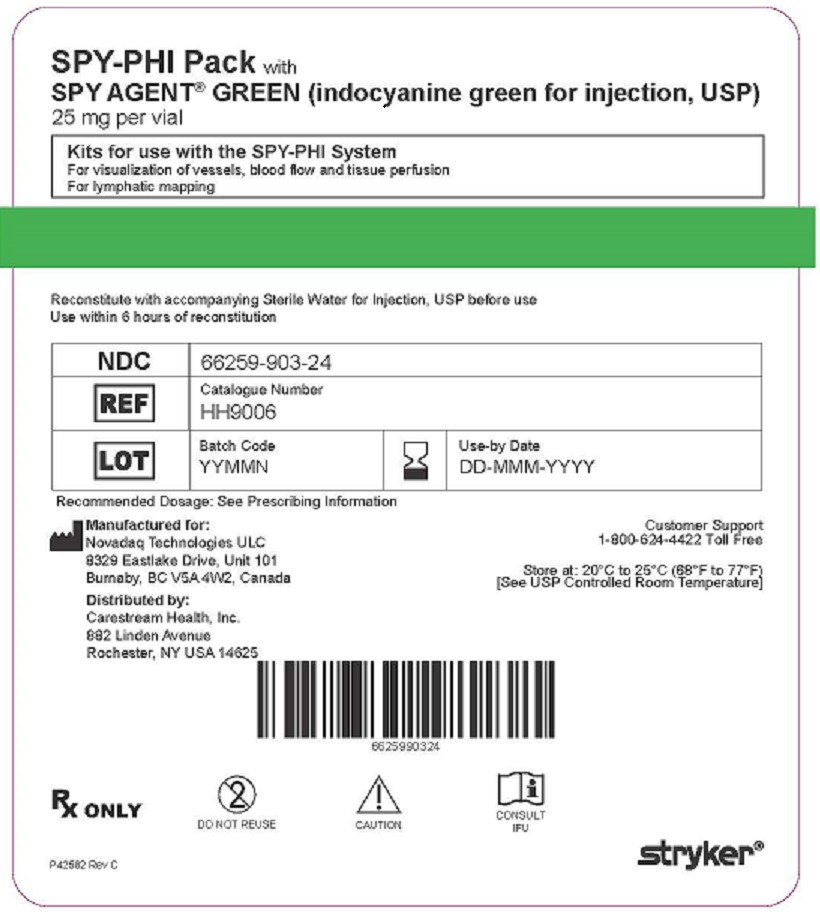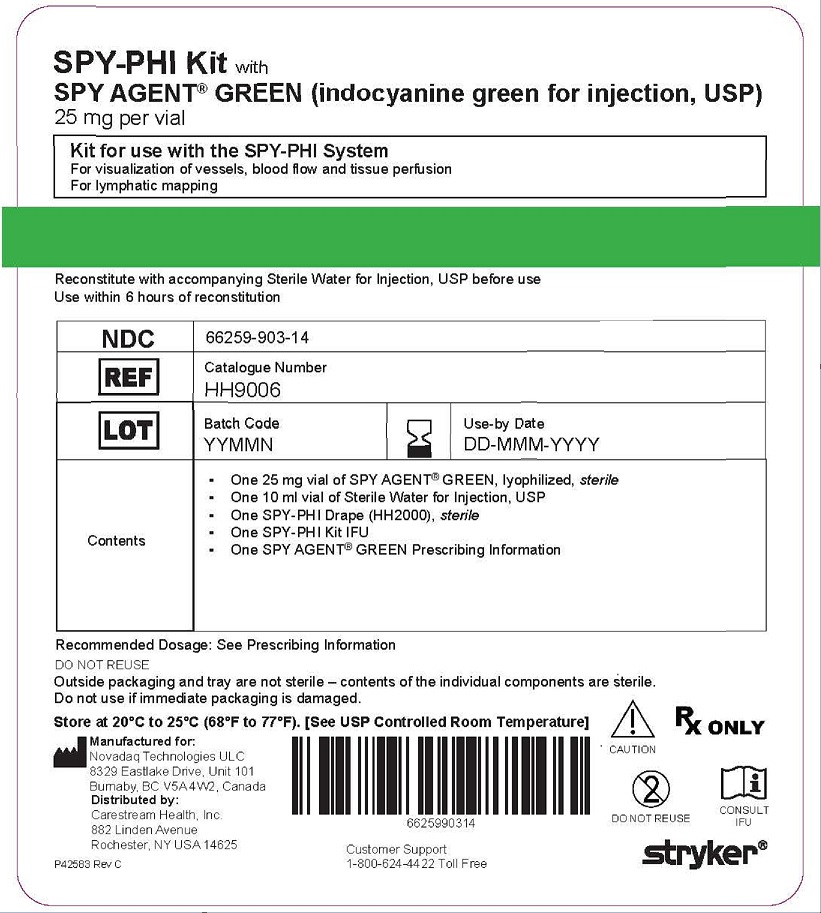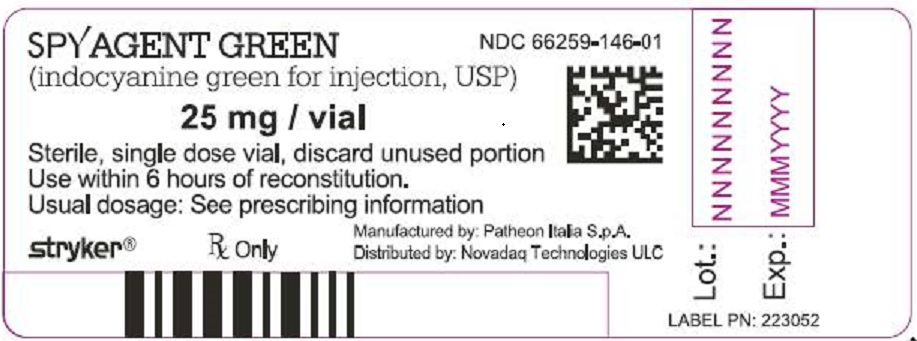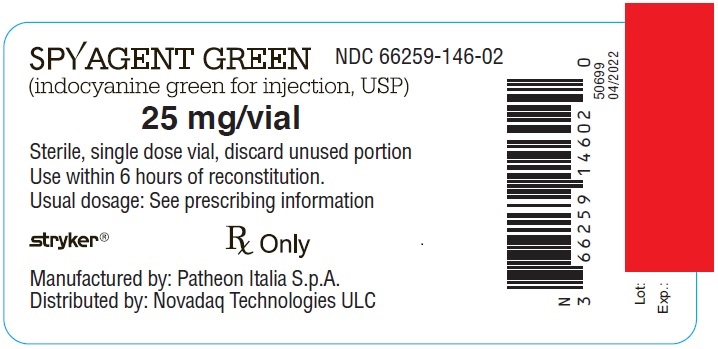 DRUG LABEL: SPY Elite Kit
NDC: 66259-306 | Form: KIT | Route: INTRAVENOUS
Manufacturer: Novadaq Technologies Inc
Category: prescription | Type: HUMAN PRESCRIPTION DRUG LABEL
Date: 20230615

ACTIVE INGREDIENTS: WATER 1 mL/1 mL; INDOCYANINE GREEN 25 mg/1 1
INACTIVE INGREDIENTS: SODIUM IODIDE

HIGHLIGHTS OF PRESCRIBING INFORMATION

These highlights do not include all the information needed to use SPY AGENT GREEN safely and effectively. See full prescribing information for SPY AGENT GREEN.
SPY AGENT® GREEN (indocyanine green for injection), for intravenous, interstitial, or intradermal use
Initial U.S. Approval: 1959

RECENT MAJOR CHANGES

Indications and Usage (1.4) | 06/2023
Dosage and Administration (2.4) | 06/2023

1 INDICATIONS AND USAGE

SPY AGENT GREEN is an optical imaging agent indicated for use with a fluorescence imaging device for:

- Visualization of vessels (micro and macro vasculature), blood flow and tissue perfusion before, during, and after vascular, gastrointestinal, organ transplant, plastic, micro- and reconstructive surgeries including general minimally invasive surgical procedures in adults and pediatric patients one month of age and older. (1.1)
- Visualization of extrahepatic biliary ducts in adults and pediatric patients aged 12 years and older. (1.2)
- Visualization of lymph nodes and lymphatic vessels during lymphatic mapping in adults with cervical and uterine cancer. (1.3)
- Visualization of lymph nodes and lymphatic vessels during lymphatic mapping in adults with breast cancer. (1.4)

2 DOSAGE AND ADMINISTRATION

- Visualization of vessels, blood flow and tissue perfusion (2.5 mg/mL solution)
  - 1.25 mg to 5 mg by intravenous injection is recommended for a surgical procedure in adults and pediatric patients aged 1 month and older.
  - 3.75 mg to 10 mg by intravenous injection is recommended for visualization of perfusion in extremities through the skin for plastic, micro- and reconstructive surgeries in adults.
  - Additional doses may be administered. Do not exceed a total dose of 2 mg/kg. (2.1)

- Visualization of extrahepatic biliary ducts in adults and pediatric patients aged 12 years and older (2.5 mg/mL solution)
  - 2.5 mg by intravenous injection at least 45 minutes prior to surgery.
  - Additional doses may be administered. Do not exceed a total dose of 2 mg/kg. (2.2)

- Lymphatic mapping of cervical and uterine cancer in adults (1.25 mg/mL solution)
  - 5 mg interstitially as four 1 mL injections.
  - See Full Prescribing Information for injection techniques. (2.3)

- Lymphatic mapping of breast cancers in adults (2.5 mg/mL solution)
  - 0.25 mg per breast intradermally as two 0.05 mL peri-areolar injections.
  - A subsequent peri-tumoral dose of 0.375 mg per breast (three 0.05 mL injections) may be administered intradermally.
  - See Full Prescribing Information for injection techniques. (2.4)

- See Full Prescribing Information for reconstitution instructions. (2.5).

3 DOSAGE FORMS AND STRENGTHS

For injection: 25 mg indocyanine green as a lyophilized, green powder for reconstitution in a single-patient-use vial. (3)

4 CONTRAINDICATIONS

Hypersensitivity to indocyanine green. (4)

5 WARNINGS AND PRECAUTIONS

Hypersensitivity reactions: Hypersensitivity reactions including anaphylaxis and urticaria have occurred. Always have cardiopulmonary resuscitation personnel and equipment readily available and monitor patients. (5.1)

6 ADVERSE REACTIONS

Lymphatic mapping of breast cancers: Most common adverse reactions were skin and injection site discoloration in two patients (1.4%). (6.1)

To report SUSPECTED ADVERSE REACTIONS, contact Stryker Corp. at 1-800-624-4422 or FDA at 1-800-FDA-1088 or www.fda.gov/medwatch.

7 DRUG INTERACTIONS

Interference with Thyroid Radioactive Iodine Uptake Studies: Do not perform radioactive iodine uptake studies for at least a week following the use of SPY AGENT GREEN. (7)

FULL PRESCRIBING INFORMATION

1 INDICATIONS AND USAGE

1.1 Visualization of Vessels, Blood Flow and Tissue Perfusion

SPY AGENT GREEN is indicated for fluorescence imaging of vessels (micro- and macro-vasculature), blood flow and tissue perfusion before, during and after vascular, gastrointestinal, organ transplant, plastic, micro- and reconstructive surgeries, including general minimally invasive surgical procedures in adults and pediatric patients aged 1 month and older.

1.2 Visualization of Extrahepatic Biliary Ducts

SPY AGENT GREEN is indicated for fluorescence imaging of extrahepatic biliary ducts in adults and pediatric patients aged 12 years and older.

1.3 Lymphatic Mapping of Cervical and Uterine Cancer

SPY AGENT GREEN is indicated for fluorescence imaging of lymph nodes and delineation of lymphatic vessels during lymphatic mapping in adults with cervical and uterine cancer for which this procedure is a component of intraoperative management.

1.4 Lymphatic Mapping of Breast Cancer

SPY AGENT GREEN is indicated for fluorescence imaging of lymph nodes and delineation of lymphatic vessels during lymphatic mapping in adults with breast cancer for which this procedure is a component of intraoperative management.

2 DOSAGE AND ADMINISTRATION

2.1 Recommended Dose, Administration and Imaging for Visualization of Vessels, Blood Flow and Tissue Perfusion

Dosing
Adults:
The recommended dose of SPY AGENT GREEN for a single image sequence for visualization of vessels, blood flow and tissue perfusion in adults is 1.25 mg to 5 mg administered intravenously as 0.5 mL to 2 mL of a 2.5 mg/mL solution.

For visualization of perfusion in extremities through the skin in adults, the recommended dose is 3.75 mg to 10 mg administered intravenously as 1.5 mL to 4 mL of a 2.5 mg/mL solution.

Immediately flush with a 10 mL bolus of 0.9% Sodium Chloride Injection, USP.

Pediatric patients aged 1 month and older:
The recommended dose of SPY AGENT GREEN for a single image sequence for visualization of vessels, blood flow and tissue perfusion in pediatric patients aged 1 month and older is 1.25 mg to 5 mg administered intravenously as 0.5 mL to 2 mL of a 2.5 mg/mL solution. Lower doses may be administered in younger patients and in those with lower body weight. Adjust the amount and type of flush to avoid volume and/or sodium overload.

In both adults and pediatric patients aged 1 month and older, additional doses may be administered to obtain imaging sequences during the procedure. Do not exceed the maximum total dose of 2 mg/kg.

Administration
Prior to the imaging procedure, draw up the desired dose of SPY AGENT GREEN solution into appropriate syringes and prepare a 10 mL syringe of 0.9% Sodium Chloride Injection, USP.

Administer via a central or peripheral venous line using a three-way stopcock attached to an injection port on the infusion line. Inject the prepared SPY AGENT GREEN into the line as a tight bolus. Immediately switch the access on the stopcock and inject the prepared flush.

Imaging Instructions
SPY AGENT GREEN may be used with either the SPY® Elite or PINPOINT® Fluorescence Imaging Systems or with a FDA cleared or approved imaging device that is specifically indicated for use with indocyanine green for fluorescence imaging of vessels, blood flow and tissue perfusion.

A fluorescence response should be visible in blood vessels within 5 seconds to 15 seconds after injection.

2.2 Recommended Dose, Administration and Imaging for Visualization of Extrahepatic Biliary Ducts

Dosing and Administration
The recommended dose of SPY AGENT GREEN for visualization of extrahepatic biliary ducts in adults and pediatric patients aged 12 years and older is 2.5 mg administered intravenously as 1 mL of a 2.5 mg/mL solution at least 45 minutes prior to surgery.

Additional doses may be administered to obtain imaging sequences during the procedure. Do not exceed a total dose of 2 mg/kg.

Imaging Instructions
SPY AGENT GREEN may be used with the PINPOINT® Fluorescence Imaging System or with a FDA cleared or approved imaging device that is specifically indicated for use with indocyanine green for fluorescence imaging of extrahepatic biliary ducts.

Fluorescence is visible in the biliary tree within 45 minutes after injection.

2.3 Recommended Dose, Administration and Imaging for Lymphatic Mapping of Cervical and Uterine Cancer

Dosing and Administration
The recommended dose of SPY AGENT GREEN for lymphatic mapping of cervical and uterine cancer in adults is 5 mg administered interstitially as four 1 mL injections of a 1.25 mg/mL solution into the cervix, at the 3 o’ clock and the 9 o’clock positions with a superficial (1 mm to 3 mm) and a deep (1 cm to 3 cm) injection at each position.

Imaging Instructions
SPY AGENT GREEN may be used with the PINPOINT® Fluorescence Imaging System or with a FDA cleared or approved imaging device that is specifically indicated for use with indocyanine green for fluorescence imaging of lymph nodes and delineation of lymphatic vessels during lymphatic mapping of cervical and uterine cancer.

Fluorescent lymphatic vessels and lymph nodes should begin to be visible within 1 minute after injection.

2.4 Recommended Dose, Administration and Imaging for Lymphatic Mapping of Breast Cancer

Dosing and Administration
The recommended dose of SPY AGENT GREEN for lymphatic mapping of breast cancer in adults is 0.25 mg per breast administered intradermally as two 0.05 mL injections of a 2.5 mg/mL solution into the peri-areolar area at the 12 o’clock and the 9 o’clock positions for the right breast or at the 12 o’clock and 3 o’clock positions for the left breast.

If lymphatic flow towards the axillary lymph nodes is not visualized, a subsequent peri-tumoral dose of 0.375 mg (three 0.05 mL injections intradermally at the 12 o’clock, 3 o’clock and 9 o’clock positions) is recommended.

Imaging Instructions
SPY AGENT GREEN may be used during open field surgery with the SPY Portable Handheld Imaging (SPY-PHI®) System or with a FDA cleared or approved imaging device that is specifically indicated for use with indocyanine green for fluorescence imaging of lymph nodes and delineation of lymphatic vessels during lymphatic mapping of breast cancer.

Fluorescent lymphatic vessels and lymph nodes should begin to be visible within 1 minute after injection.

2.5 Reconstitution Instructions

General

- Prepare SPY AGENT GREEN under sterile conditions prior to surgery.
- Inspect the reconstituted solution for particulate matter. The reconstituted solution should be a clear, green solution.
- Use the prepared solution within 6 hours.
- Discard any unused product.

Visualization of Vessels, Blood Flow, Tissue Perfusion and Extrahepatic Biliary Ducts and Lymphatic Mapping of Breast Cancer
Dissolve SPY AGENT GREEN with 10 mL Sterile Water for Injection, USP to form a concentration of 2.5 mg indocyanine green/mL.

Lymphatic Mapping of Cervical and Uterine Cancer
Dissolve SPY AGENT GREEN with 20 mL Sterile Water for Injection, USP to form a concentration of 1.25 mg indocyanine green/mL.

3 DOSAGE FORMS AND STRENGTHS

For injection: 25 mg of indocyanine green as a sterile, lyophilized, green powder for reconstitution provided in a 20 mL or a 25 mL single-patient-use vial.

4 CONTRAINDICATIONS

SPY AGENT GREEN is contraindicated in patients with a history of hypersensitivity to indocyanine green. Reactions have included anaphylaxis [see Warnings and Precautions (5.1)] .

5 WARNINGS AND PRECAUTIONS

5.1 Hypersensitivity Reactions

Hypersensitivity reactions including anaphylaxis, urticaria and deaths due to anaphylaxis have been reported following intravenous administration of indocyanine green [see Adverse Reactions (6.2)]. SPY AGENT GREEN is contraindicated in patients with a history of hypersensitivity to indocyanine green [see Contraindications (4)]. Always have cardiopulmonary resuscitation personnel and equipment readily available and monitor all patients for hypersensitivity reactions.

5.2 Interference with Thyroid Radioactive Iodine Uptake Studies

Because SPY AGENT GREEN contains iodine, the iodine-binding capacity of thyroid tissue may be reduced for at least one week following administration [see Drug Interactions (7)].

6 ADVERSE REACTIONS

The following adverse reactions are discussed in greater detail in other sections of the label:

- Hypersensitivity Reactions [see Warnings and Precautions (5.1)] .

6.1 Clinical Trials Experience

Because clinical trials are conducted under widely varying conditions, adverse reaction rates observed in the clinical trials of a drug cannot be directly compared to rates in the clinical trials of another drug and may not reflect the rates observed in practice.

Lymphatic Mapping of Breast Cancer

In an open-label, single arm, clinical trial, 151 patients with breast cancer received a single dose of 0.25 mg SPY AGENT GREEN intradermally into the peri-areolar area. Five patients received a subsequent peri-tumoral injection of 0.375 mg intradermally in addition to the peri-areolar dose of 0.25 mg [see Clinical Studies (14.2)].

Skin discoloration including injection site discoloration were reported in two patients (1.4%).

6.2 Postmarketing Experience

The following adverse reactions have been identified during post-approval use of indocyanine green products including SPY AGENT GREEN. Because these reactions are reported voluntarily from a population of uncertain size, it is not always possible to reliably estimate their frequency or establish a causal relationship to drug exposure.

Immune System Disorders: Anaphylaxis, urticaria.

7 DRUG INTERACTIONS

Interference with Thyroid Radioactive Iodine Uptake Studies

Because SPY AGENT GREEN contains iodine, the iodine-binding capacity of thyroid tissue may be reduced for at least one week following administration. Do not perform radioactive iodine uptake studies for at least one week following administration of SPY AGENT GREEN.

8 USE IN SPECIFIC POPULATIONS

8.1 Pregnancy

Risk Summary
There are no adequate and well-controlled studies of SPY AGENT GREEN in pregnant women. Available data from a very small number of scientific literature studies with indocyanine green use in pregnant women over several decades have not reported any drug associated risks for major birth defects, miscarriage, or adverse maternal or fetal outcomes. Data from one small study in which indocyanine green was administered intravenously to pregnant women during labor suggest there is no placental transfer of the drug. Animal reproduction studies have not been conducted with indocyanine green.

All pregnancies have a background risk of birth defects, loss, or other adverse outcomes. In the U.S. general population, the estimated background risk of major birth defects and miscarriage in clinically recognized pregnancies is 2 to 4% and 15 to 20%, respectively.

8.2 Lactation

Risk Summary
Seventeen cases of indocyanine green use in lactating women have been reported in the scientific literature with no adverse events observed in the breastfed infant. However, there are no data on the presence of indocyanine green in human milk or the effects on milk production. Therefore, the developmental and health benefits of breastfeeding should be considered along with the mother's clinical need for SPY AGENT GREEN and any potential adverse effects on the breastfed infant from SPY AGENT GREEN or from the underlying maternal condition.

8.4 Pediatric Use

Use of SPY AGENT GREEN for visualization of vessels, blood flow and tissue perfusion has been established in pediatric patients aged 1 month and older. Pediatric use is supported by published data in 49 pediatric patients who received indocyanine green for assessment of blood flow and tissue perfusion in cardiovascular, vascular, plastic, micro- and reconstructive surgical procedures, and by clinical trials in adults. No overall differences in safety or effectiveness have been observed between pediatric patients and adults. The dose range was similar to the effective dose range in adults [See Dosage and Administration (2.1)]. The use of SPY AGENT GREEN for visualization of vessels, blood flow and tissue perfusion has not been established in pediatric patients aged less than 1 month.

Use of SPY AGENT GREEN for visualization of extrahepatic biliary ducts has been established in pediatric patients aged 12 years and older. Pediatric use is supported by clinical trials in adults in addition to clinical use in pediatric patients. No overall differences in safety or effectiveness have been observed between pediatric patients and adults. The dose range was similar to the effective dose range in adults [See Dosage and Administration (2.2)]. The use of SPY AGENT GREEN for visualization of extrahepatic biliary ducts has not been established in pediatric patients aged less than 12 years.

The safety and efficacy of SPY AGENT GREEN for visualization of lymph nodes and lymphatic vessels during lymphatic mapping for cervical and uterine cancer and breast cancer have not been established in pediatric patients.

8.5 Geriatric Use

Of the total number of patients in clinical studies of SPY AGENT GREEN in visualization of vessels, blood flow and tissue perfusion, 7% were 65 and over, while 1% were 75 and over. Of the total number of patients in clinical studies of SPY AGENT GREEN in visualization of lymph nodes and lymphatic vessels during lymphatic mapping of cervical and uterine cancer, 9% were 65 and over, while 2% were 75 and over. Of the total number of patients in clinical studies of SPY AGENT GREEN in visualization of lymph nodes and lymphatic vessels during lymphatic mapping of breast cancer, 38% were 65 and over, while 8% were 75 and over.

No overall differences in safety or effectiveness were observed between these patients and younger patients, and other reported clinical experience has not identified differences in responses between elderly and younger patients.

Clinical studies of SPY AGENT GREEN in visualization of extrahepatic biliary ducts did not include sufficient numbers of patients aged 65 and over to determine whether they respond differently from younger patients. Other reported clinical experience has not identified differences in responses between elderly and younger patients.

In general, dose selection for an elderly patient should be cautious, usually starting at the low end of the dosing range, reflecting the greater frequency of decreased hepatic, renal, or cardiac function, and of concomitant disease or other drug therapy.

11 DESCRIPTION

SPY AGENT GREEN (indocyanine green for injection, USP) is a water soluble, optical imaging agent which is reconstituted with Sterile Water for Injection, USP, for intravenous, interstitial or intradermal use. Each vial contains a sterile, lyophilized, green powder containing 25 mg of indocyanine green with not more than 5% sodium iodide. Hydrochloric acid or sodium hydroxide may be used to adjust the pH prior to lyophilization.

The chemical name for Indocyanine Green is 1 HBenz[e]indolium, 2-[7-[1,3-dihydro-1,1-dimethyl-3-(4-sulfobutyl)-2H-benz[e] indol-2-ylidene]-1,3,5-heptatrienyl]-1,1-dimethyl-3-(4-sulfobutyl)-, hydroxide, inner salt, sodium salt.

Molecular Formula: C 43H 47N 2NaO 6S 2; Molecular Mass: 774.96 g/mol, with the following structural formula:

Indocyanine green has a peak spectral absorption at 805 nm. SPY AGENT GREEN has a pH of 5.5 to 7.5 when reconstituted with Sterile Water for Injection, USP.

12 CLINICAL PHARMACOLOGY

12.1 Mechanism of Action

When bound to proteins in plasma or in lymph fluid, indocyanine green absorbs light in the near infrared region with peak absorption at 805 nm and emits fluorescence (light) at a slightly longer wavelength, with peak emission at 830 nm. Fluorescence imaging devices provide external energy as near infrared light for indocyanine green to absorb, resulting in excitation of the indocyanine green, and the emitted light (fluorescence) is transferred from the field of view to an image on a monitor. These optical properties of indocyanine green are utilized in fluorescence imaging of the micro- and macro vasculature, blood flow and tissue perfusion, the extrahepatic biliary ducts, and for lymphatic mapping of lymph nodes and lymphatic vessels.

12.2 Pharmacodynamics

There is no relevant pharmacodynamic data.

12.3 Pharmacokinetics

Distribution
Following intravenous injection, indocyanine green binds to plasma proteins (98%) and is largely confined to the intravascular compartment. Indocyanine green undergoes no significant extrahepatic or enterohepatic circulation; simultaneous arterial and venous blood estimations have shown negligible renal, peripheral, lung or cerebro-spinal uptake of the dye. After biliary obstruction, the dye appears in the hepatic lymph, independently of the bile, suggesting that the biliary mucosa is sufficiently intact to prevent diffusion of the dye, though allowing diffusion of bilirubin.

Following interstitial or intradermal injections, indocyanine green binds to proteins in lymph fluid and the interstitial space, is taken up by the lymphatic vessels, and drains to the lymph nodes.

Elimination
Indocyanine green is taken up from the plasma almost exclusively by the hepatic parenchymal cells and is secreted entirely into the bile.

14 CLINICAL STUDIES

14.1 Lymphatic Mapping of Cervical and Uterine Cancer

The FILM Study (NCT 02209532) was a randomized, prospective, multi-center, open-label study in patients with early stage uterine or cervical cancer and no known regional nodal or metastatic disease by standard clinical evaluation. SPY AGENT GREEN and a blue dye comparator were injected into the cervix of patients at the beginning of the operative procedure.

A total of 176 patients were randomized to receive either SPY AGENT GREEN followed by blue dye or blue dye followed by SPY AGENT GREEN. Four 1 mL injections of a 1.25 mg/mL solution of SPY AGENT GREEN for a total dose of 5 mg were administered interstitially into the cervix at the 3 o’clock and 9 o’clock positions with a superficial (1 mm to 3 mm) and a deep (1 cm to 3 cm) injection at each position.

Lymphatic mapping was performed intraoperatively using the PINPOINT® Fluorescence Imaging System and standard light, followed by excision of tissues identified by SPY AGENT GREEN, blue dye, or the surgeon’s visual and palpation examination. The resected tissues were evaluated by histopathology to confirm presence of lymph nodes. The efficacy of SPY AGENT GREEN and the PINPOINT® Fluorescence Imaging System in the detection of lymphatic vessels and lymph nodes during lymphatic mapping procedures was determined by the number of histology-confirmed lymph nodes detected by SPY AGENT GREEN and/or the blue dye comparator.

The mean age of the 176 patients was 63 years (range: 31 to 88 years); distribution by race and ethnicity was 79% White, 4% Black or African American, 3% Asian, 13% Hispanic/Latino and 1% other.

Table 1 shows the distribution of resected, confirmed lymph nodes detected by SPY AGENT GREEN or blue dye in the modified intent-to-treat population (mITT). Among the confirmed lymph nodes identified, 93% were identified using SPY AGENT GREEN, and 43% were identified using blue dye, a difference of 50% [95% confidence interval 39% to 60%].

Table 1: Distribution of Resected Confirmed Lymph Nodes Detected by SPY AGENT GREEN or Blue Dye (BD)
Analysis Population | Nodes (n) | All Lymph Nodes Detected with SPY AGENT GREEN | All Lymph Nodes Detected with BD | Lymph Nodes Detected with SPY AGENT GREEN Only | Lymph Nodes Detected with BD Only | Lymph Nodes Detected with Neither
mITT | 513 | (476/513) 93% | (220/513) 43% | (262/513) 51% | (6/513) 1% | (31/513) 6%

Table 2 shows the number of patients with at least one resected, confirmed lymph node and the number of patients with at least one bilateral lymph node pair detected by SPY AGENT GREEN or blue dye. With SPY AGENT GREEN, approximately 97% of patients had at least one resected, confirmed lymph node detected and 73% had at least one bilateral lymph node pair detected, compared with 68% and 28%, respectively, with blue dye [p-values for each analysis <0.0001].

Table 2: Distribution of Patients with at Least One Confirmed Unilateral Lymph Node / Bilateral Pair Detected by SPY AGENT GREEN or Blue Dye (BD)
Analysis Population | Patients (n) | Patients with All Lymph Nodes Detected with SPY AGENT GREEN | Patients with All Lymph Nodes Detected with BD | Patients with Lymph Nodes Detected with SPY AGENT GREEN Only | Patients with Lymph Nodes Detected with BD Only | Patients with Lymph Nodes Detected with Neither
mITT Unilateral* | 172 | (167/172) 97% | (118/172) 68% | (51/172) 30% | (2/172) 1% | (3/172) 3%
mITT Bilateral** | 172 | (126/172) 73% | (49/172) 28% | (79/172) 46% | (2/172) 1% | (44/172) 26%
*: patients with at least one resected confirmed lymph node detected unilaterally
**: patients with at least one resected confirmed lymph node detected bilaterally

14.2 Lymphatic Mapping of Breast Cancer

The FILM-B Study (NCT 03200704) was a single-arm, prospective, multi-center, open-label, non inferiority study in 151 patients with early stage breast cancer with clinically negative nodal status who were scheduled for surgery that included clinically indicated sentinel lymph node biopsy with approved Tc 99m-labeled active comparators.

Patients were administered SPY AGENT GREEN at the beginning of the operative procedure and an active comparator the day before or the day of surgery. There were no patients with bilateral breast cancer, therefore, a single index breast was injected in all patients. Two 0.05 mL injections of a 2.5 mg/mL solution of SPY AGENT GREEN for a total dose of 0.25 mg were administered intradermally into the peri areolar region of the index breast at the 12 o’clock and 9 o’clock positions for the right breast and at the 12 o’clock and 3 o’clock positions for the left breast. Five patients received a subsequent peri-tumoral dose consisting of three intradermal injections of 0.05 mL each at the 12 o’clock, 3 o’clock and 9 o’clock positions for a total dose of 0.375 mg. Three of these five patients had unsuccessful lymphatic mapping and received a full axillary lymph node dissection. Lymphatic mapping was performed intraoperatively using the SPY-PHI® System followed by use of a handheld gamma probe as well as the surgeon’s visual and palpation examination. The resected tissues were evaluated by histopathology to confirm presence of lymph nodes.

The mean age of the 151 patients was 60 years (range: 25 to 84 years); distribution by race and ethnicity was 81% White, 7% Black or African American, 5% Asian, 3% Hispanic/Latino and 3% other.

The efficacy of SPY AGENT GREEN in the detection of lymphatic vessels and lymph nodes during lymphatic mapping procedures was determined by the number of histology-confirmed lymph nodes detected by SPY AGENT GREEN followed by use of a gamma probe.

Table 3 shows the percentage of resected, confirmed lymph nodes and the percentage of patients with at least one resected, confirmed lymph node detected by SPY AGENT GREEN.

Table 3: Detection of Resected, Confirmed Lymph Nodes by SPY AGENT GREEN at the Node-Level and the Patient-Level
Lymph Nodes/ Patients (n) | Number (Percentage) of Lymph Nodes Detected with SPY AGENT GREEN | Number (Percentage) of Patients with at Least One Lymph Node Detected with SPY AGENT GREEN
406†/151 | 360 (89%) | 145 (96%)
†Lymph nodes resected by using the SPY-PHI System and a handheld gamma probe as well as the surgeon’s visual and palpation examination.

SPY AGENT GREEN met the prespecified noninferiority margin of 5% relative to active comparator at the node-level.

16 HOW SUPPLIED/STORAGE AND HANDLING

SPY AGENT GREEN (indocyanine green for injection, USP) is supplied as 25 mg of lyophilized powder in a 20 mL (NDC 66259-146-01) or 25 mL (NDC 66259-146-02) single-patient-use vial in the following configurations:

Spy Elite Kit; NDC 66259-306-13; Kit for use with SPY Elite System; For visualization of vessels, blood flow, and tissue perfusion | One 25 mg SPY AGENT GREEN (Indocyanine Green for Injection, USP) vial,; One 10 mL Sterile Water for Injection, USP plastic vial,; One ND8000 sterile drape
Spy Elite Pack; NDC 66259-306-23 | 6 SPY Elite kits:; Six 25 mg SPY AGENT GREEN (Indocyanine Green for Injection, USP) vials,; Six 10 mL Sterile Water for Injection, USP plastic vials,; Six ND8000 sterile drapes
SPY-PHI Kit; NDC 66259-903-14; Kit for use with SPY-PHI System For visualization of vessels, blood flow, and tissue perfusion; For lymphatic mapping | One 25 mg SPY AGENT GREEN (Indocyanine Green for Injection, USP) vial,; One 10 mL Sterile Water for Injection, USP plastic vial,; One SPY-PHI (HH2000) sterile drape
SPY-PHI Pack; NDC 66259-903-24 | 6 SPY-PHI kits:; Six 25 mg SPY AGENT GREEN (Indocyanine Green for Injection, USP) vials,; Six 10 mL Sterile Water for Injection, USP plastic vials,; Six SPY-PHI (HH2000) sterile drapes
SPY Minimally Invasive Surgery (SPY-MIS) Kit; NDC 66259-936-15; Kit for use with Advanced Imaging Modality (AIM) and PINPOINT Systems For visualization of vessels, blood flow, and tissue perfusion For visualization of extrahepatic biliary ducts | One 25 mg SPY AGENT GREEN (Indocyanine Green for Injection, USP) vial,; One 10 mL Sterile Water for Injection, USP plastic vial,; Two 3 mL syringes (sterile),; Two 10 mL syringes (sterile),; Two 18G, 1 inch needles (sterile),; Labels for syringes
SPY Minimally Invasive Surgery (SPY-MIS) Pack; NDC 66259-936-25 | 6 SPY-MIS kits:; Six 25 mg SPY AGENT GREEN (Indocyanine Green for Injection, USP) vials,; Six 10 mL Sterile Water for Injection, USP plastic vials,; Twelve 3 mL syringes (sterile),; Twelve 10 mL syringes (sterile),; Twelve 18G, 1 inch needles (sterile),; Labels for syringes
SPY Lymphatics Kit; NDC 66259-937-16; Kit for use with Advanced Imaging Modality (AIM) L10 and L11 Light Sources and 1688 Camera System, and the PINPOINT System For lymphatic mapping | One 25 mg SPY AGENT GREEN (Indocyanine Green for Injection, USP) vial,; Two 10 mL Sterile Water for Injection, USP plastic vials,; One 10 mL syringe (sterile),; One luer-lock 10 mL syringe with controlled handle (sterile),; Two spinal needles 22G, 3.5 inch (sterile),; Labels for syringes
SPY Lymphatics Pack; NDC 66259-937-26 | 6 SPY Lymphatics kits:; Six 25 mg SPY AGENT GREEN (Indocyanine Green for Injection, USP) vials,; Twelve 10 mL Sterile Water for Injection, USP plastic vials,; Six 10 mL syringes (sterile),; Six luer-lock 10 mL syringes with controlled handle (sterile),; Twelve spinal needles 22G, 3.5 inch (sterile),; Labels for syringes

NDC 63323-185-10 (or NDC 0409-4887-10) Sterile Water for Injection, USP, 10 mL fill in 10 mL plastic vials.

STORAGE AND HANDLING

STORAGE: Store at 20°C to 25°C (68°F to 77°F) [See USP Controlled Room Temperature].

17 PATIENT COUNSELING INFORMATION

Hypersensitivity Reactions

Advise patients to seek medical attention for reactions following injection of SPY AGENT GREEN such as difficulty breathing, swollen tongue or throat, skin reactions including hives, itching and flushed or pale skin, low blood pressure, a weak and rapid pulse and other symptoms or signs of an anaphylactic reaction [see Warnings and Precautions (5.1)].

Manufactured by:
Patheon Italia S.p.A.
Ferentino (FR) or Monza (MB), Italy

Distributed by:
Novadaq Technologies ULC
8329 Eastlake Drive, Unit 101,
Burnaby, BC, Canada V5A 4W2

Sterile Water for Injection, USP is manufactured by:
Fresenius Kabi USA, LLC
Grand Island, NY 14072 U.S.A.
or
Hospira, Inc.
Rocky Mount, NC 27804 U.S.A.

LB0016-05